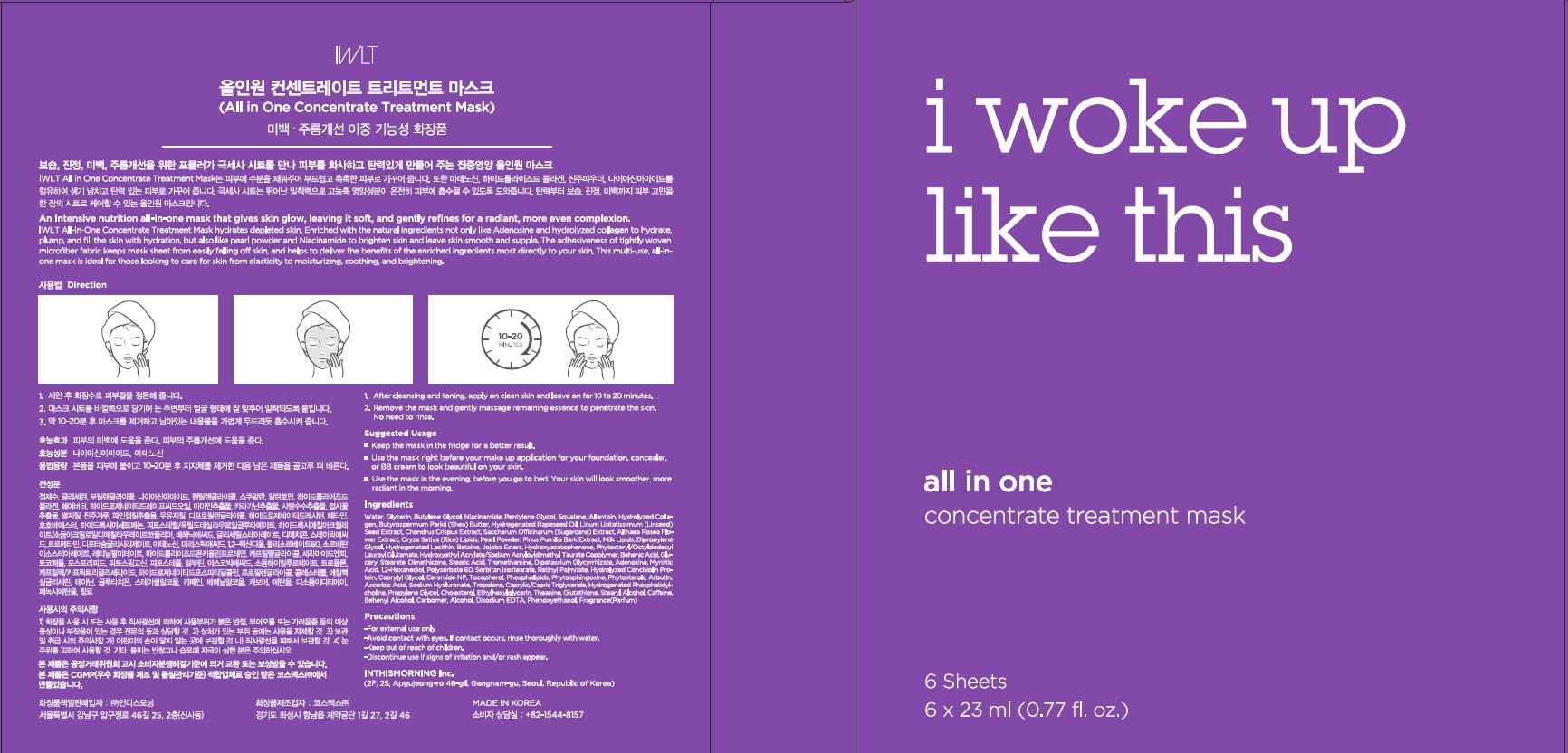 DRUG LABEL: all in one concentrate treatment mask
NDC: 71217-0038 | Form: LIQUID
Manufacturer: In This Morning
Category: otc | Type: HUMAN OTC DRUG LABEL
Date: 20200102

ACTIVE INGREDIENTS: ADENOSINE 0.04 g/100 mL; NIACINAMIDE 3 g/100 mL
INACTIVE INGREDIENTS: WATER; BUTYLENE GLYCOL

Drug Facts

ACTIVE INGREDIENT

niacinamide, adenosine

INACTIVE INGREDIENT

Water
Butylene Glycol
Glycerin
Glycosaminoglycans
Viscum Album (Mistletoe) Leaf Extract
Lactobacillus/Soybean Ferment Extract
Imperata Cylindrica Root Extract
Oryza Sativa (Rice) Extract
Palmaria Palmata Extract
Selaginella Lepidophylla Extract
Algae Extract
Lactobacillus Ferment
Fructan
Beta-Glucan
Sodium Hyaluronate
Hydrolyzed Hyaluronic Acid
Sclerocarya Birrea Seed Oil
Oryza Sativa (Rice) Germ Oil
Citrus Paradisi (Grapefruit) Peel Oil
Citrus Aurantium Dulcis (Orange) Oil
Cedrus Atlantica Bark Oil
Lavandula Angustifolia (Lavender) Oil
Litsea Cubeba Fruit Oil
Pelargonium Graveolens Flower Oil
Elettaria Cardamomum Seed Oil
Santalum Album (Sandalwood) Oil
Maltodextrin
Phospholipids
Hydroxyacetophenone
Ethylhexylglycerin
Caprylyl Glycol
1,2-Hexanediol
Octyldodeceth-16
Caprylic/Capric Triglyceride

PURPOSE

for elasticity to moisturizing, soothing, and brightening

keep out or reach of the children

INDICATIONS AND USAGE

after cleansing and toning, apply on clean skin and leave on for 10 to 20 minutes

remove the mask and gently massage remaining essence to penetrate the skin, no need to rinse

WARNINGS

1. Do not use in the following cases(Eczema and scalp wounds)
2.Side Effects
1)Due to the use of this druf if rash, irritation, itching and symptopms of hypersnesitivity occur dicontinue use and consult your phamacisr or doctor
3.General Precautions
1)If in contact with the eyes, wash out thoroughty with water If the symptoms are servere, seek medical advice immediately
2)This product is for exeternal use only. Do not use for internal use
4.Storage and handling precautions
1)If possible, avoid direct sunlight and store in cool and area of low humidity
2)In order to maintain the quality of the product and avoid misuse
3)Avoid placing the product near fire and store out in reach of children

DOSAGE AND ADMINISTRATION

for external use only